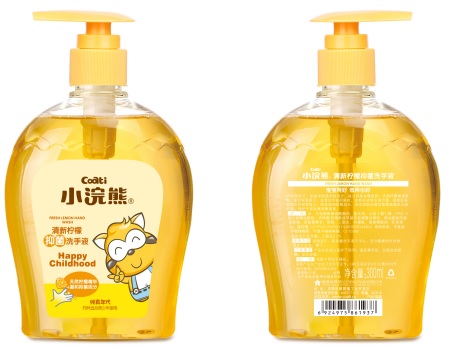 DRUG LABEL: Antibacterial Hand Wash
NDC: 74531-002 | Form: SOLUTION
Manufacturer: Fujian Mengjiaolan Daily Chemical Co., Ltd.
Category: otc | Type: HUMAN OTC DRUG LABEL
Date: 20200330

ACTIVE INGREDIENTS: SILVER 0.18 mg/300 mL
INACTIVE INGREDIENTS: SODIUM LAURETH SULFATE; SORBITOL; WATER

Antibacterial Hand Wash

The Hand Wash is manufactured using only the following United States Pharmacopoeia (USP) grade ingredients in the preparation of the product (percentage in final product formulation) :

1. SILVER 0.18mg/300ml
2. SODIUM LAURETH SULFATE
3. SORBITOL
4. Sterile distilled water or boiled cold water.

The firm does not add other active or inactive ingredients. Different or additional ingredients may impact the quality and potency of the product.

Active Ingredient(s)

SILVER 0.18mg/300ml Purpose: Antiseptic

Purpose

Antiseptic, Hand Sanitizer

Use

Hand Sanitizer to help reduce bacteria that potentially can cause disease. For use when soap and water are not available.

Warnings

For external use only. Flammable. Keep away from heat or flame

Do not use

- in children less than 2 months of age
- on open skin wounds

When using this product keep out of eyes, ears, and mouth. In case of contact with eyes, rinse eyes thoroughly with water.
Stop use and ask a doctor if irritation or rash occurs. These may be signs of a serious condition.
Keep out of reach of children. If swallowed, get medical help or contact a Poison Control Center right away.

Stop use and ask a doctor if irritation or rash occurs. These may be signs of a serious condition.

Keep out of reach of children. If swallowed, get medical help or contact a Poison Control Center right away.

Directions

- Place enough product on hands to cover all surfaces. Rub hands together until dry.
- Supervise children under 6 years of age when using this product to avoid swallowing.

Other information

- Store between 15-30C (59-86F)
- Avoid freezing and excessive heat above 40C (104F)

Inactive ingredients

SODIUM LAURETH SULFATE, SORBITOL, purified water USP

Package Label - Principal Display Panel

300 mL NDC: 74531-002-01